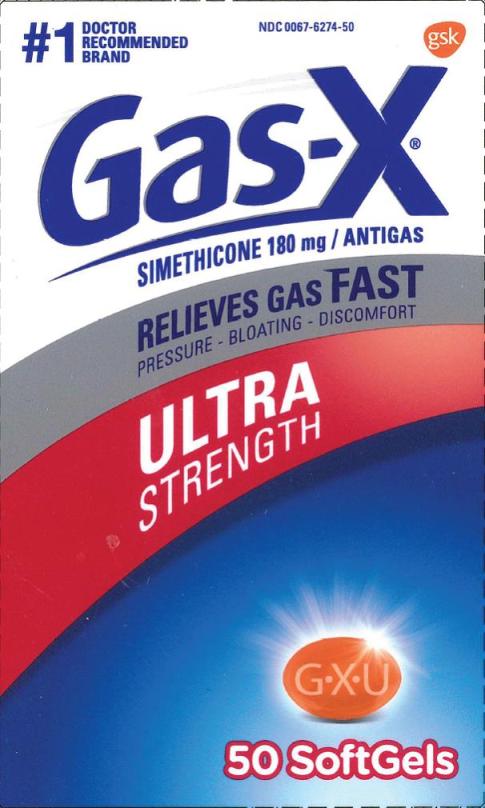 DRUG LABEL: Gas-X

NDC: 0067-6274 | Form: CAPSULE, LIQUID FILLED
Manufacturer: Haleon US Holdings LLC
Category: otc | Type: HUMAN OTC DRUG LABEL
Date: 20240405

ACTIVE INGREDIENTS: DIMETHICONE 180 mg/1 1
INACTIVE INGREDIENTS: SILICON DIOXIDE; FD&C YELLOW NO. 6; GELATIN, UNSPECIFIED; GLYCERIN; HYPROMELLOSE, UNSPECIFIED; LIGHT MINERAL OIL; MANNITOL; PEPPERMINT OIL; WATER; SORBITOL; LECITHIN, SOYBEAN; TITANIUM DIOXIDE

Drug Facts

Active ingredient (in each softgel)

Simethicone 180 mg

Purpose

Antigas

Use

for the relief of

- pressure and bloating commonly referred to as gas

Directions

- adults: swallow with water 1 or 2 softgels as needed after meals and at bedtime
- do not exceed 2 softgels in 24 hours except under the advice and supervision of a physician

Other information

- store at a controlled room temperature 20-25°C (68-77°F)
- protect from heat and moisture

Inactive ingredients

FD&C yellow 6, gelatin, glycerin, hypromellose, light mineral oil, mannitol, peppermint oil, purified water, sorbitol, soy lecithin, titanium dioxide

Questions or comments?

Call 1-800-452-0051

Principal Display Panel

#1 DOCTOR RECOMMENDED BRAND

NDC 0067-6274-50

Gas-X®

SIMETHICONE 180 mg/ ANTIGAS

RELIEVES GAS FAST

PRESSURE • BLOATING • DISCOMFORT

ULTRA STRENGTH

50 SoftGels

Gas-X®Ultra Strength Softgels are concentrated to contain liquid gas-fighting medicine in a small softgel so they are easy to swallow, and there is no chalky taste.

TAMPER EVIDENT FEATURE:

Gas-X ®Ultra Strength Softgels are sealed in blister packets. Use only if the individual seal is unbroken.

Gas-X®Ultra Strength Softgels offer fast, effective relief of pressure and bloating that antacids can’t provide. They are specially formulated with simethicone, the antigas medicine doctors recommend most for pressure, bloating or discomfort referred to as gas.

1-800-452-0051

www.Gas-X.com

Distributed by:

GSK Consumer Healthcare

- Warren, NJ 07059

Trademarks are owned by or licensed to the GSK group of companies.

©2016 GSK group of companies or its licensor. All rights reserved.

46177347